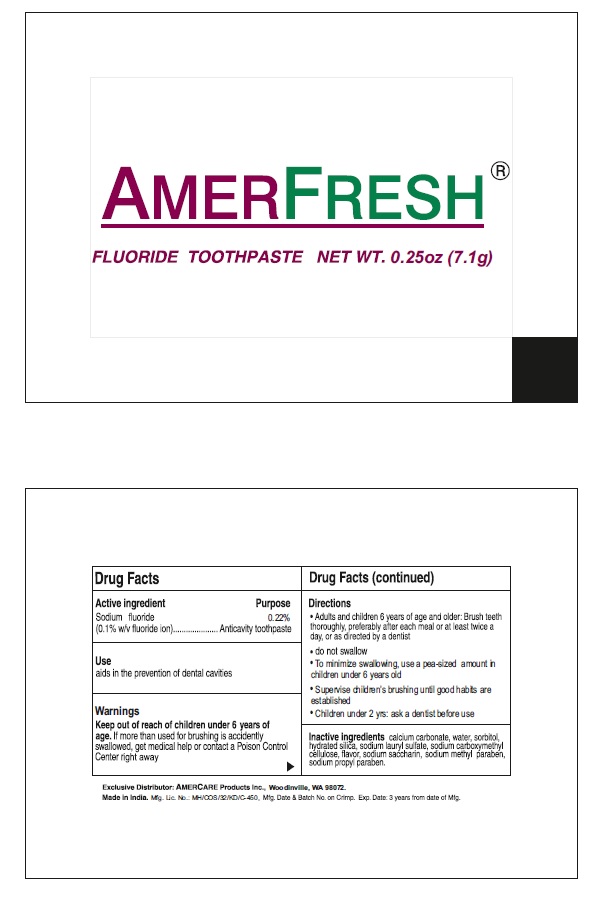 DRUG LABEL: AMERFRESH
NDC: 73398-114 | Form: PASTE
Manufacturer: SUHAN AEROSOL
Category: prescription | Type: HUMAN PRESCRIPTION DRUG LABEL
Date: 20201203

ACTIVE INGREDIENTS: SODIUM FLUORIDE 2.2 mg/1 g
INACTIVE INGREDIENTS: CALCIUM CARBONATE; WATER; SORBITOL; HYDRATED SILICA; SODIUM LAURYL SULFATE; CARBOXYMETHYLCELLULOSE SODIUM, UNSPECIFIED; SACCHARIN SODIUM; METHYLPARABEN SODIUM; PROPYLPARABEN SODIUM

AMERFRESH FLUORIDE TOOTHPASTE

Active Ingredients

Sodium fluoride-0.22%

Purpose

Anticavity Toothpaste.

Uses

aids in the prevention of dental cavities

Warnings

- Keep out of the reach of children under 6 years of age .
- If more than used for brushing is accidently swallowed ,get medical help or contact a Poison Control Center right away.

Directions

- Adults and children 6 years of age and older .Brush teeth thoroughly ,preferably after each meal or at least twice a day,or as directed by a dentist.
- Do not swallow.
- To minimize the swallowing ,use a pea-sized amount in children under 6 years old.
- Supervise children’s brushing until good habits are established.
- Children under 2 yrs : ask a dentist before use

Inactive Ingredients

Calcium Carbonate, Water,Sorbitol,Hydrated Silica, Sodium Lauryl Sulphate,Sodium Carboxymethyl cellulose, Flavor, Sodium Saccharin, Sodium methyl paraben, Sodium propyl paraben.